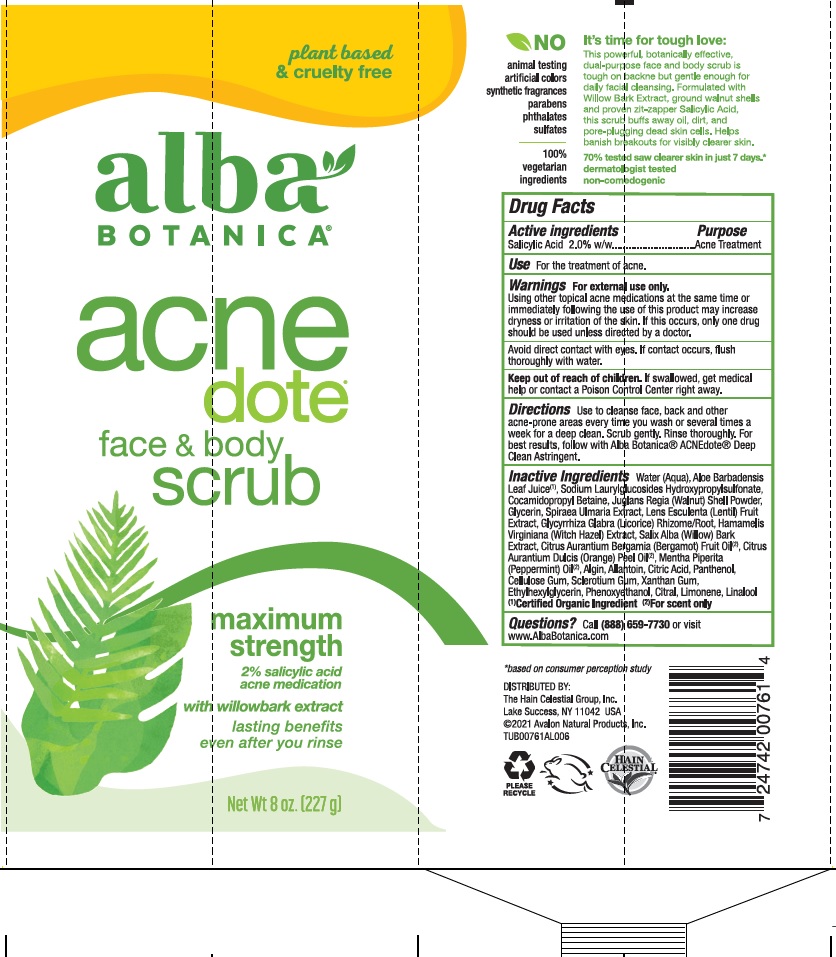 DRUG LABEL: AL00761 Alba Botanica Acnedote Face and Body Scrub
NDC: 61995-3761 | Form: CREAM
Manufacturer: The Hain Celestial Group, Inc.
Category: otc | Type: HUMAN OTC DRUG LABEL
Date: 20240731

ACTIVE INGREDIENTS: SALICYLIC ACID 2 g/100 g
INACTIVE INGREDIENTS: BERGAMOT OIL; CITRAL; LIMONENE, (+)-; FILIPENDULA ULMARIA WHOLE; LENTIL; WITCH HAZEL; ORANGE PEEL; PEPPERMINT OIL; ALGINIC ACID; JUGLANS REGIA SHELL; SODIUM HYDROXYPROPYLSULFONATE LAURYLGLUCOSIDE-7 CROSSPOLYMER; COCAMIDOPROPYL BETAINE; LICORICE; ETHYLHEXYLGLYCERIN; CARBOXYMETHYLCELLULOSE SODIUM; PANTHENOL; SALIX ALBA BARK; WATER; GLYCERIN; ALOE VERA LEAF; CITRIC ACID MONOHYDRATE; PHENOXYETHANOL; LACTIC ACID; XANTHAN GUM; CLAVICEPS PURPUREA SCLEROTIUM; LINALOOL, (+)-

AL00761 Alba Botanica AcneDote Face and Body Scrub
Formula PF161846-08

Active Ingredient

Salicylic Acid 2.0%

DOSAGE AND ADMINISTRATION

Use to cleanse face, back and other acne-prone areas every time you wash or several times a week for a deep clean. Scrub gently. Rinse thoroughly.

PURPOSE

Acne Treatment

WARNINGS

Using other topical acne medications at the same time or immediately following the use of this product may increase dryness or irritation of the skin. If this occurs, only one drug should be used unless directed by a doctor. Avoid direct contact with eyes. If contact occurs, flush throughly with water.

Keep out of reach of children. If swallowed get medical help or contact Poison Center right away.

INACTIVE INGREDIENT

Aqua (Water)

Aloe Barbadensis Leaf Juice (1)

Sodium Laurylglucosides Hydroxypropylsulfonate

Cocamidopropyl Betaine

Juglans Regia (Walnut) Shell Powder

Glycerin

Spiraea Ulmaria Extract

Lens Esculenta (Lentil) Fruit Extract

Glycyrrhiza Glabra (Licorice) Rhizome/Root

Hamamelis Virginiana (Witch Hazel) Extract

Salix Alba (Willow) Bark Extract

Citrus Aurantium Bergamia (Bergamot) Fruit Oil (2)

Citrus Aurantium Dulcis (Orange) Peel Oil (2)

Mentha Piperita (Peppermint) Oil (2)

Algin

Citric Acid

Panthenol

Cellulose Gum

Sclerotium Gum

Xanthan Gum

Ethylhexylglycerin

Phenoxyethanol

Citral

Limonene

Linalool

(1) Certified Organic Ingredient; ((2) Natural Fragrance

INDICATIONS AND USAGE

For the treatment of acne.

Stop use and ask a doctor if irritation occurs.

OTHER SAFETY INFORMATION

N/A

QUESTIONS

Call (888) 659-7730

WHEN USING

N/A